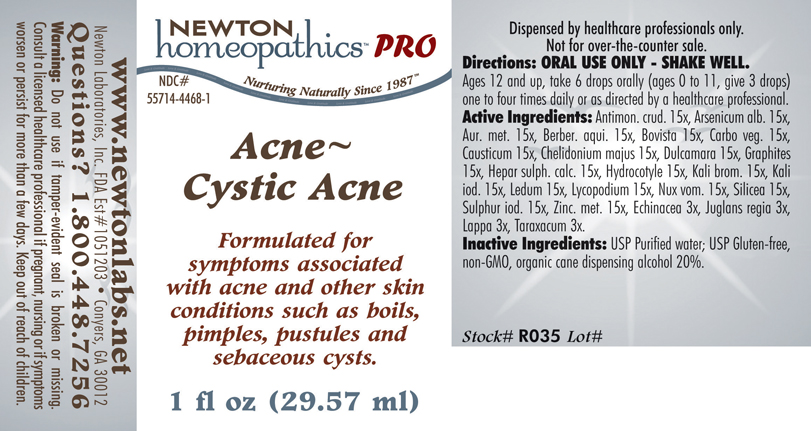 DRUG LABEL: Acne Cystic Acne 
NDC: 55714-4468 | Form: LIQUID
Manufacturer: Newton Laboratories, Inc.
Category: homeopathic | Type: HUMAN PRESCRIPTION DRUG LABEL
Date: 20110601

ACTIVE INGREDIENTS: Antimony Trisulfide 15 [hp_X]/1 mL; Arsenic Trioxide 15 [hp_X]/1 mL; Gold 15 [hp_X]/1 mL; Mahonia Aquifolium Root Bark 15 [hp_X]/1 mL; Giant Puffball 15 [hp_X]/1 mL; Activated Charcoal 15 [hp_X]/1 mL; Causticum 15 [hp_X]/1 mL; Chelidonium Majus 15 [hp_X]/1 mL; Solanum Dulcamara Top 15 [hp_X]/1 mL; Graphite 15 [hp_X]/1 mL; Calcium Sulfide 15 [hp_X]/1 mL; Centella Asiatica 15 [hp_X]/1 mL; Potassium Bromide 15 [hp_X]/1 mL; Potassium Iodide 15 [hp_X]/1 mL; Ledum Palustre Twig 15 [hp_X]/1 mL; Lycopodium Clavatum Spore 15 [hp_X]/1 mL; Strychnos Nux-vomica Seed 15 [hp_X]/1 mL; Silicon Dioxide 15 [hp_X]/1 mL; Sulfur Iodide 15 [hp_X]/1 mL; Zinc 15 [hp_X]/1 mL; Echinacea, Unspecified 3 [hp_X]/1 mL; English Walnut 3 [hp_X]/1 mL; Arctium Lappa Root 3 [hp_X]/1 mL; Taraxacum Officinale 3 [hp_X]/1 mL

Acne~Cystic Acne

PRODUCT NAME & INDICATIONS SECTION

ACNE~CYSTIC ACNE Formulated for symptoms associated with acne and other skin conditions such as boils, pimples, pustules and sebaceous cysts.

DIRECTION SECTION

Directions: ORAL USE ONLY - SHAKE WELL. Ages 12 and up, take 6 drops (ages 0 to 11, give 3 drops) one to four times daily or as directed by a healthcare professional.

ACTIVE INGREDIENT SECTION

Antimon. crud. 15x, Arsenicum alb.5x, Aur. met. 15x, Berber. aqui. 15x, Bovista 15x, Carbo veg. 15x, Causticum 15x, Chelidonium majus 15x, Dulcamara 15x, Graphites 15x, Hepar sulph. calc. 15x, Hydrocotyle 15x, Kali brom. 15x, Kali iod. 15x, Ledum 15x, Lycopodium 15x, Nux vom. 15x, Silicea 15x, Sulphur iod. 15x, Zinc. met. 15x, Echinacea 3x, Juglans regia 3x, Lappa 3x, Taraxacum 3x.

PURPOSE SECTION

Formulated for symptoms associated with acne and other skin conditions such as boils, pimples, pustules and sebaceous cysts.

INACTIVE INGREDIENT SECTION

Inactive Ingredients: USP Purified Water; USP Gluten-free, non-GMO, organic cane dispensing alcohol 20%.

QUESTIONS? SECTION

www.newtonlabs.net Newton Laboratories, Inc. FDA Est # 1051203 - Conyers, GA 30012
Questions? 1.800.448.7256

WARNINGS SECTION

Warning: Do not use if tamper - evident seal is broken or missing. Consult a licensed healthcare professional if pregnant, nursing or if symptoms worsen or persist for more than a few days. Keep out of reach of children.

PREGNANCY OR BREAST FEEDING SECTION

Consult a licensed healthcare professional if pregnant or nursing or if symptoms worsen or persist for more than a few days.

KEEP OUT OF REACH OF CHILDREN SECTION

Keep out of reach of children.